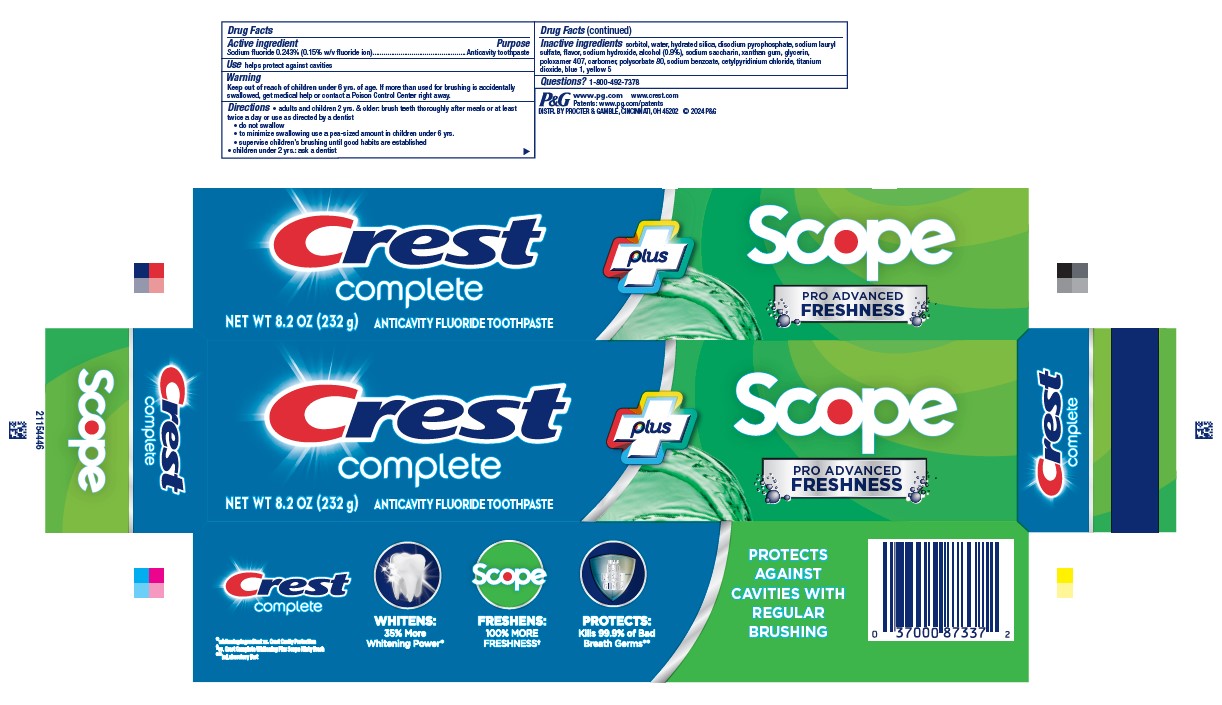 DRUG LABEL: Crest Complete plus
NDC: 84126-614 | Form: PASTE, DENTIFRICE
Manufacturer: The Procter & Gamble Manufacturing Company
Category: otc | Type: HUMAN OTC DRUG LABEL
Date: 20260107

ACTIVE INGREDIENTS: SODIUM FLUORIDE 1.5 mg/1 g
INACTIVE INGREDIENTS: SODIUM HYDROXIDE; SACCHARIN SODIUM; GLYCERIN; POLOXAMER 407; SODIUM ACID PYROPHOSPHATE; SODIUM LAURYL SULFATE; ALCOHOL; XANTHAN GUM; CARBOXYPOLYMETHYLENE; POLYSORBATE 80; SODIUM BENZOATE; CETYLPYRIDINIUM CHLORIDE; SORBITOL; FD&C BLUE NO. 1; WATER; HYDRATED SILICA; TITANIUM DIOXIDE; FD&C YELLOW NO. 5

Crest Complete Plus Scope Pro Advanced Freshness

Drug Facts

Active ingredient

Sodium fluoride 0.243%

(0.15% w/v fluoride ion)

Purpose

Anticavity toothpaste

Use

helps protect against cavities

Warnings

Keep out of reach of children under 6 yrs. of age.If more than used for brushing is accidentally swallowed, get medical help or contact a Poison Control Center right away.

Directions

- adults and children 2 yrs. & older: brush teeth thoroughly after meals or at least twice a day or use as directed by a dentist
  - do not swallow
  - to minimize swallowing use a pea-sized amount in children under 6
  - supervise children's brushing until good habits are established
- children under 2 yrs.: ask a dentist

Inactive ingredients

sorbitol, water, hydrated silica, disodium pyrophosphate, sodium lauryl
sulfate, flavor, sodium hydroxide, alcohol (0.9%), sodium saccharin, xanthan gum, glycerin,
poloxamer 407, carbomer, polysorbate 80, sodium benzoate, cetylpyridinium chloride, titanium
dioxide, blue 1, yellow 5

Questions?

1-800-492-7378

DISTR. BY PROCTER & GAMBLE,
CINCINNATI, OH 45202

PRINCIPAL DISPLAY PANEL - 232 g Carton

Crest

Complete

New Wt 8.2 OZ (232 g)

Anticavity Fluoride Toothpaste

Plus

Scope

Pro Advanced

Freshness